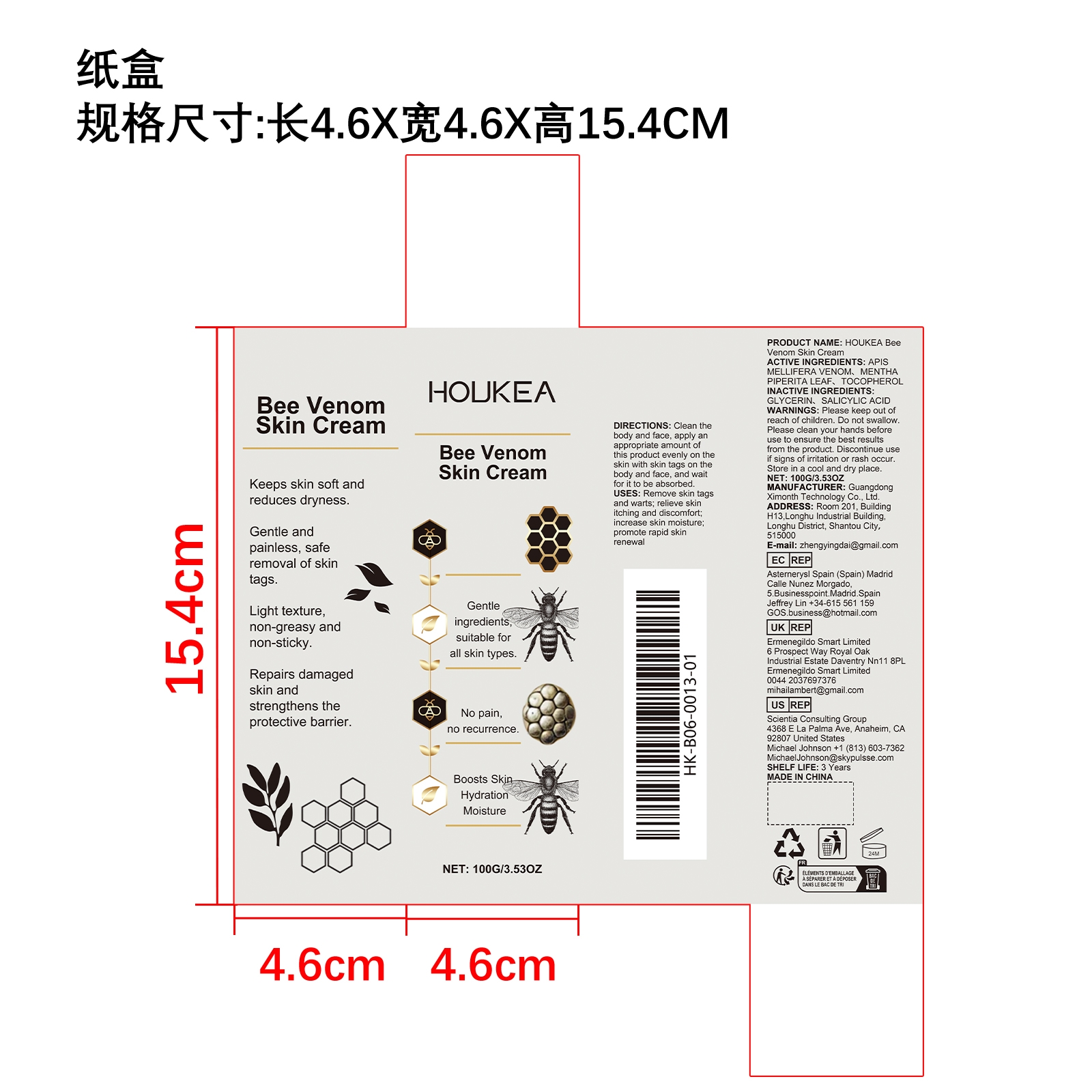 DRUG LABEL: HOUKEA Bee Venom Skin Cream
NDC: 84660-088 | Form: CREAM
Manufacturer: Guangdong Ximonth Technology Co., Ltd.
Category: otc | Type: HUMAN OTC DRUG LABEL
Date: 20241029

ACTIVE INGREDIENTS: MENTHA PIPERITA LEAF 10 g/100 g; APIS MELLIFERA VENOM 30 g/100 g; TOCOPHEROL 15 g/100 g
INACTIVE INGREDIENTS: SALICYLIC ACID 30 g/100 g; GLYCERIN 15 g/100 g

ACTIVE INGREDIENTS

APIS MELLIFERA VENOM，MENTHA PIPERITA LEAF，TOCOPHEROL

PURPOSE

Remove skin tags and warts; relieve skin itching and discomfort; increase skin moisture; promote rapid skin renewal

USES

Clean the body and face, apply an appropriate amount of this product evenly on the skin with skin tags on the body and face, and wait for it to be absorbed.

WARNINGS

Please keep out of reach of children. Do not swallow. Please clean your hands before use to ensure the best results from the product. Discontinue use if signs of irritation or rash occur. Store in a cool and dry place.

STOP USE

Discontinue use if signs of irritation or rash occur.

DO NOT USE

Discontinue use if signs of irritation or rash occur.

KEEP OUT OF REACH OF CHILDREN

Please keep out of reach of children. Do not swallow.

STORAGE AND HANDLING

Store in a cool and dry place.

INACTIVE INGREDIENT

GLYCERIN、SALICYLIC ACID